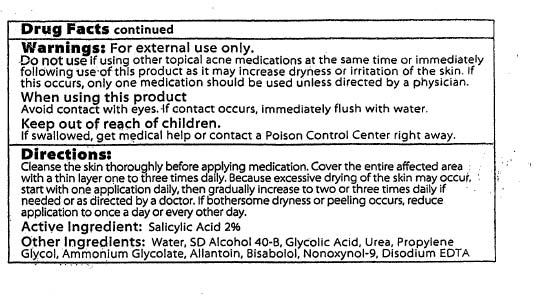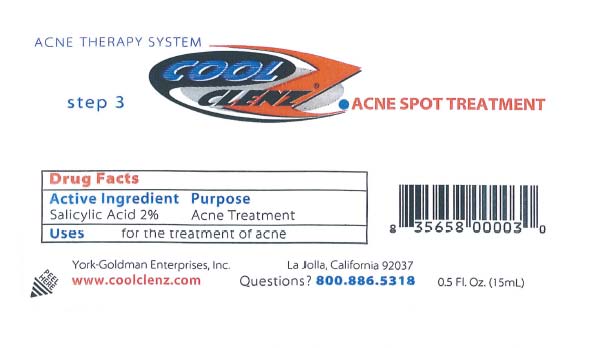 DRUG LABEL: Acni Spot
NDC: 35658-000 | Form: LIQUID
Manufacturer: La Jolla
Category: otc | Type: HUMAN OTC DRUG LABEL
Date: 20100524

ACTIVE INGREDIENTS: Salicylic Acid 1.93 mL/96.5 mL

Drug Fcts

ACTIVE INGREDIENT

Salicylic Acid 2% Acne Treatment

When using this product avoid contact with eyes. If contact occurs, immediately flush with water.

Warnings: Forexternal use only.
Do not use if using other topical acne medications at the same time or immediately
following use of this product as it may increase dryness or irritation of the skin. If
this occurs, only one medication should be used unless directed by a physician.

Keep out of reach of children.
If swallowed, get medical help or contact a Poison Control Center right away.

Directions:
Cleanse the skin thoroughly before applying medication. Cover the entire affected area
with a thin layer one to three times dally. Because excessive drying of the skin may occur,
start with one application daily, then gradually increase to two or three times daily if
needed or as directed by a doctor. If bothersome dryness or peeling occurs. reduce
application to once a day or every other day.

INACTIVE INGREDIENT

Other lngredients: Water, SD AlcohoI40-B. Glycolic Acid, Urea, Propylene
Glycol, Ammonium Glycolate, Allantoin, Bisabolol, Nonoxynol-9. Disodium EDTA

PACKAGE LABEL

pictures